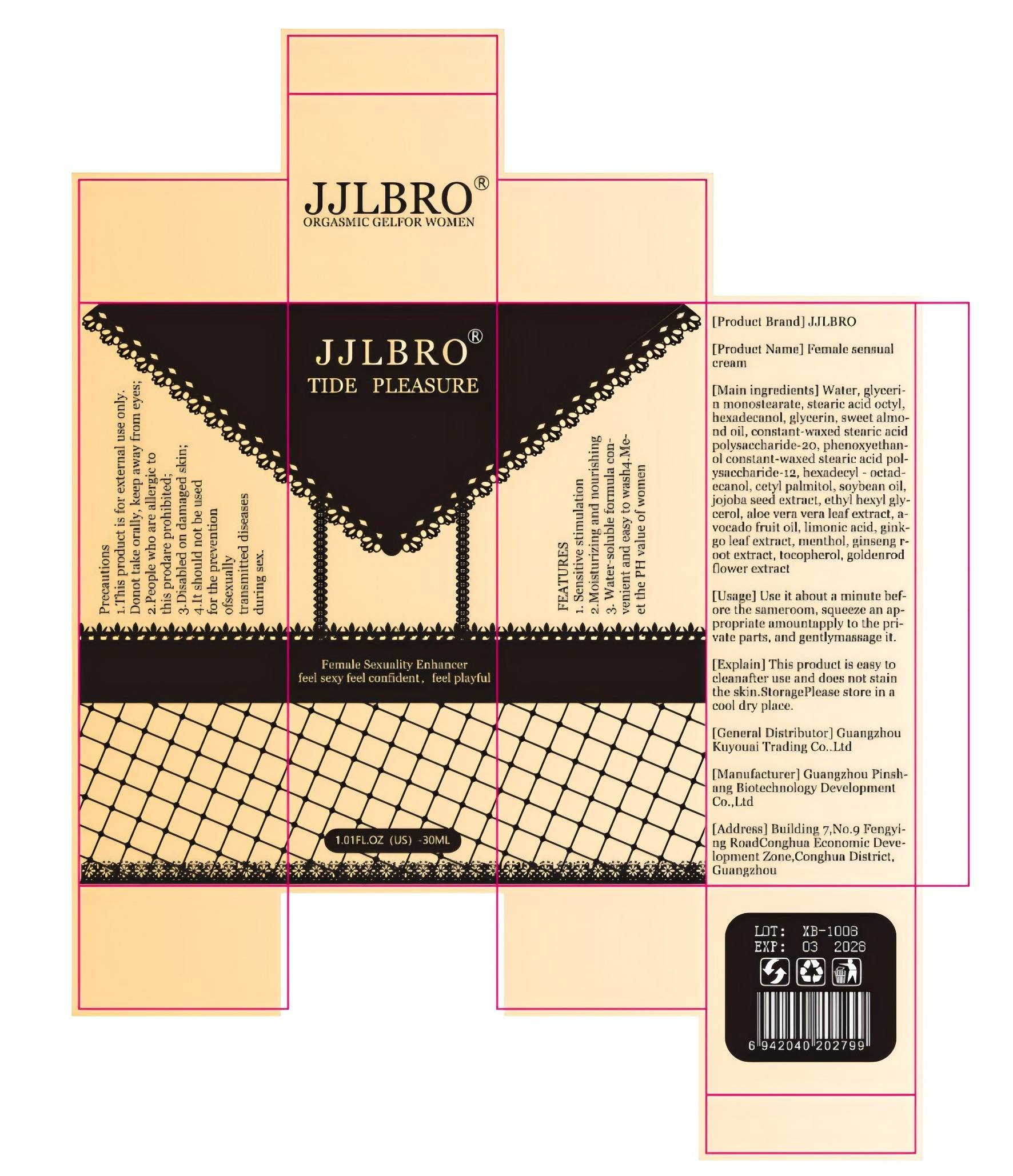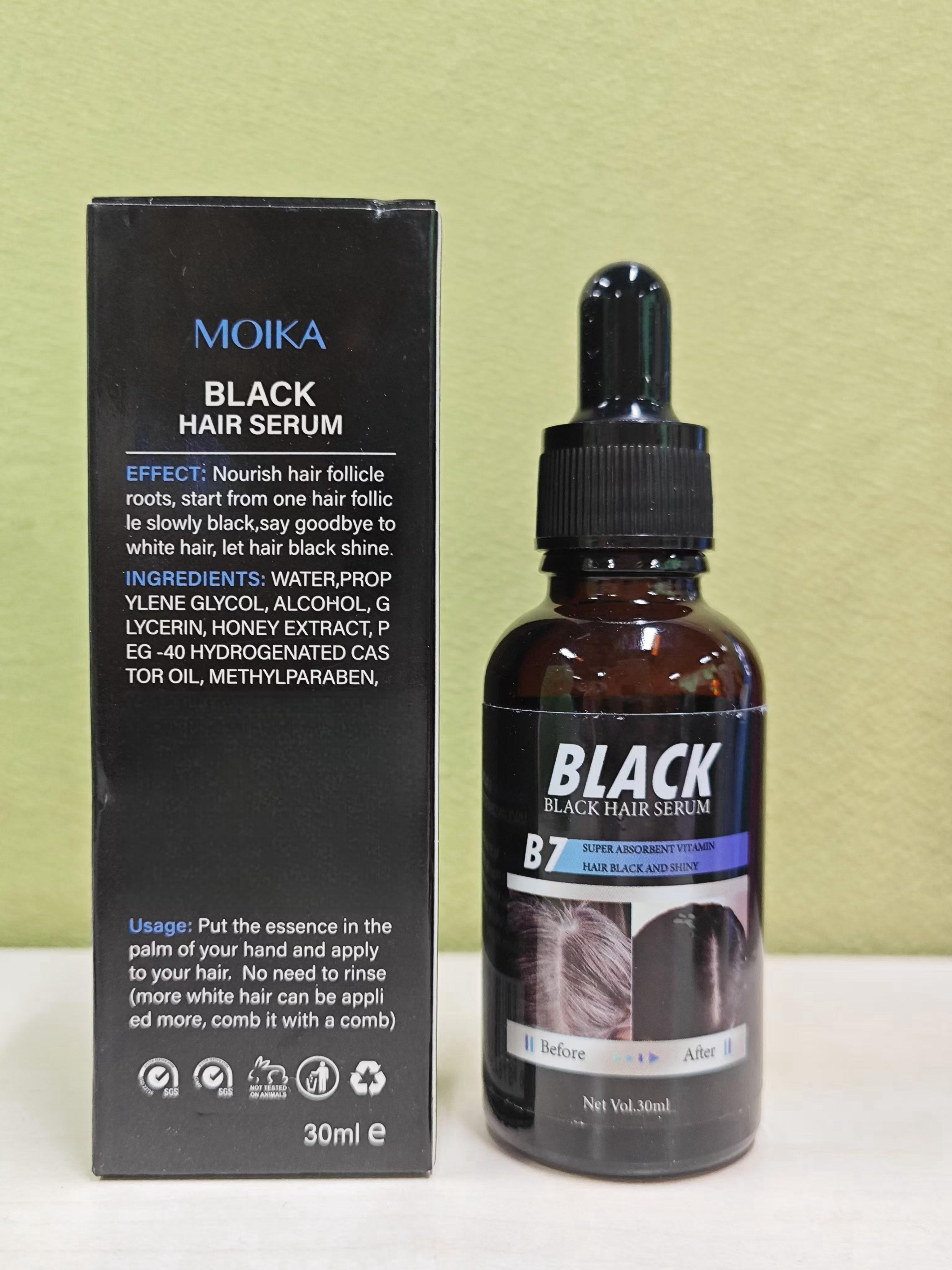 DRUG LABEL: BLACK HAIR SERUM
NDC: 84762-016 | Form: GEL
Manufacturer: Shanghai Hongmingquan Trading Co., LTD
Category: otc | Type: HUMAN OTC DRUG LABEL
Date: 20241201

ACTIVE INGREDIENTS: WATER 5 mg/5 mg
INACTIVE INGREDIENTS: PEG-40 HYDROGENATED CASTOR OIL; HONEY EXTRACT; ALCOHOL; PROPYLENE GLYCOL; GLYCERIN; METHYLPARABEN

COMPONENTS

glycerin 2mg

PURPOSE

Enhancement of women's interes

INDICATIONS AND USAGE

Apply to genitals for 5 minutes

WARNINGS

Prohibit ingestion by mouth.

Do not put into eyes or ears.

No contact with wounds.

DOSAGE AND ADMINISTRATION

For external use only.

Skin irritation occurs, wash with water, discontinue use

If symptoms do not improve, seek medical attention immediately

WHEN USING

Skin irritation occurs, wash with water, discontinue use

If symptoms do not improve, seek medical attention immediately。

Allow 5 minutes for the product to take effect

STOP USE

Wound breaks

KEEP OUT OF REACH OF CHILDREN

If sxralowed, get medical help or contact a Poison Conirol Cenler ngiht away.

INACTIVE INGREDIENT

CANDIDA ALBICANS

SOYBEAN OIL

WATER

PHENOXYETHANOL

SIMMONDSIA CHINENSIS SEED

ALOE VERA LEAF

LINOLEIC ACID

TOCOPHEROL

CETYL PALMITOLEATE

ASIAN GINSENG

GINKGO

STEARIC ACID

ETHYL HEXYL KETONE

CHAENOMELES SPECIOSA WHOLE

ALMOND OIL

AVOCADO OIL

HEXADECYLMALONIC ACID